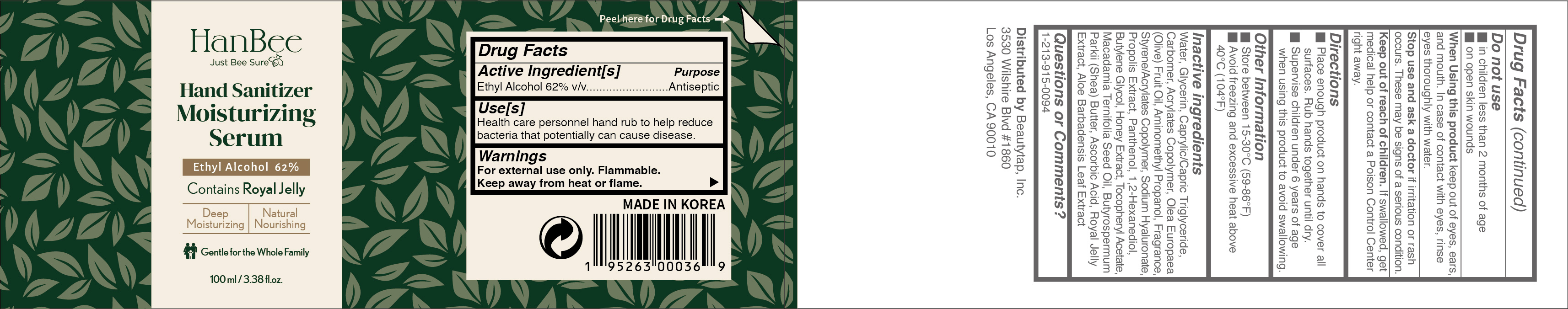 DRUG LABEL: HANBEE Hand Sanitizer Moisturizing Serum 62% 100ml
NDC: 73862-223 | Form: LOTION
Manufacturer: E.CIS Cosmetic Co.,Ltd
Category: otc | Type: HUMAN OTC DRUG LABEL
Date: 20210302

ACTIVE INGREDIENTS: ALCOHOL 62 mL/100 mL
INACTIVE INGREDIENTS: HYALURONATE SODIUM; ALOE VERA LEAF; MACADAMIA OIL; AMINOMETHYLPROPANOL; HONEY; CARBOMER 940; 1,2-HEXANEDIOL; BUTYLENE GLYCOL; .ALPHA.-TOCOPHEROL ACETATE; OLIVE OIL; MEDIUM-CHAIN TRIGLYCERIDES; ASCORBIC ACID; PANTHENOL; BUTYL ACRYLATE/METHYL METHACRYLATE/METHACRYLIC ACID COPOLYMER (18000 MW); ROYAL JELLY; GLYCERIN; WATER; SHEA BUTTER; STYRENE/ACRYLAMIDE COPOLYMER (MW 500000); PROPOLIS WAX

HANBEE Hand Sanitizer Moisturizing Serum 62% 100ml

Active Ingredient(s)

Ethyl Alcohol 62% v/v. Purpose: Antisepti

Purpose

Antiseptic, Hand Sanitizer

Use

Health care personnel hand rub to help reduce bacteria that potentially can cause disease.

Warnings

For external use only. Flammable.
Keep away from fire and flame.

Do not use

- in children less than 2 months of age
- on open skin wounds

When using this product keep out of eyes, ears, and mouth. In case of contact with eyes, rinse eyes thoroughly with water.

Stop use and ask a doctor if irritation or rash occurs. These may be signs of serious condition.

Keep out of reach of children. If swallowed, get medical help or contact a Poison Control Center right away.

Directions

- Place enough product on hands to cover all surfaces. Rub hands together until dry.
- Supervise children under 6 years of age when using this product to avoid swallowing.

Other information

- Store between 15-30C (59-86F)
- Avoid freezing and excessive heat above 40C (104F)

Inactive ingredients

Water, Cetyl Alcohol, Glycerin, Caprylic/Capric Triglyceride, Acrylates Copolymer, Olea Europaea (Olive) Fruit Oil, Carbomer, Aminomethyl Propanol, Fragrance, Styrene/Acrylates Copolymer, Sodium Hyaluronate, Propolis Extract, Panthenol, 1,2-Hexanediol, Butylene Glycol, Honey Extract, Macadamia Ternifolia Seed Oil, Butyrospermum Parkii (Shea) Butter, Ascorbic Acid, Tocopheryl Acetate, Royal Jelly Extract, Aloe Barbadensis Leaf Extract

Package Label - Principal Display Panel

HanBee
Just Bee Sure
Hand Sanitizer Moisturizing Serum
Ethyl Alcohol 62%
Contains Royal Jelly
Deep Moisturizing Natural Nourishing
Gentle for the Whole Family
100 mL (3.38 fl. oz.)